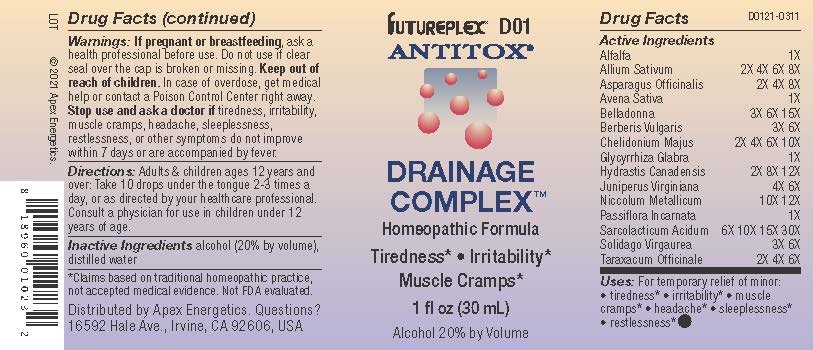 DRUG LABEL: D01
NDC: 63479-0401 | Form: SOLUTION/ DROPS
Manufacturer: Apex Energetics Inc.
Category: homeopathic | Type: HUMAN OTC DRUG LABEL
Date: 20240108

ACTIVE INGREDIENTS: SOLIDAGO VIRGAUREA FLOWERING TOP 6 [hp_X]/1 mL; ALFALFA 1 [hp_X]/1 mL; GARLIC 8 [hp_X]/1 mL; CHELIDONIUM MAJUS 10 [hp_X]/1 mL; GLYCYRRHIZA GLABRA 1 [hp_X]/1 mL; NICKEL 12 [hp_X]/1 mL; PASSIFLORA INCARNATA FLOWERING TOP 1 [hp_X]/1 mL; JUNIPERUS VIRGINIANA TWIG 6 [hp_X]/1 mL; TARAXACUM OFFICINALE 6 [hp_X]/1 mL; AVENA SATIVA FLOWERING TOP 1 [hp_X]/1 mL; GOLDENSEAL 12 [hp_X]/1 mL; LACTIC ACID, L- 30 [hp_X]/1 mL; ASPARAGUS 8 [hp_X]/1 mL; ATROPA BELLADONNA 15 [hp_X]/1 mL; BERBERIS VULGARIS ROOT BARK 6 [hp_X]/1 mL
INACTIVE INGREDIENTS: WATER; ALCOHOL

D01

Active Ingredients
Alfalfa | 1X
Allium Sativum | 2X 4X 6X 8X
Asparagus Officinalis | 2X 4X 8X
Avena Sativa | 1X
Belladonna | 3X 6X 15X
Berberis Vulgaris | 3X 6X
Chelidonium Majus | 2X 4X 6X 10X
Glycyrrhiza Glabra | 1X
Hydrastis Canadensis | 2X 8X 12X
Juniperus Virginiana | 4X 6X
Niccolum Metallicum | 10X 12X
Passiflora Incarnata | 1X
Sarcolacticum Acidum | 6X 10X 15X 30X
Solidago Virgaurea | 3X 6X
Taraxacum Officinale | 2X 4X 6X

INDICATIONS AND USAGE

Uses:

For temporary relief of minor:

tiredness*

irritability*

muscle cramps*

headache*

sleeplessness*

restlessness*

*Claims based on traditional homeopathic practice, not accepted medical evidence. Not FDA evaluated.

Warnings:

PREGNANCY OR BREAST FEEDING

If pregnant or breastfeeding, ask a health professional before use.

Do not use if clear seal over the cap is broken or missing.

Keep out of reach of children. In case of overdose, get medical help or contact a Poison Control Center right away.

Stop use and ask a doctor if tiredness, irritability, muscle cramps, headache, sleeplessness, restlessness, or other symptoms do not improve within 7 days or are accompanied by fever.

Directions:

Adults & children ages 12 years and over: Take 10 drops under the tongue 2-3 times a day, or as directed by your healthcare professional. Consult a physician for use in children under 12 years of age.

Inactive Ingredients

alcohol (20% by volume), distilled water

Distributed by Apex Energetics. Questions?

16592 Hale Ave., Irvine, CA 92606, USA

PACKAGE LABEL

FUTUREPLEX® D01

ANTITOX®

DRAINAGE COMPLEX™

Homeopathic Formula

Tiredness*

Irritability*

Muscle Cramps*

1 fl oz (30 mL)

Alcohol 20% by Volume